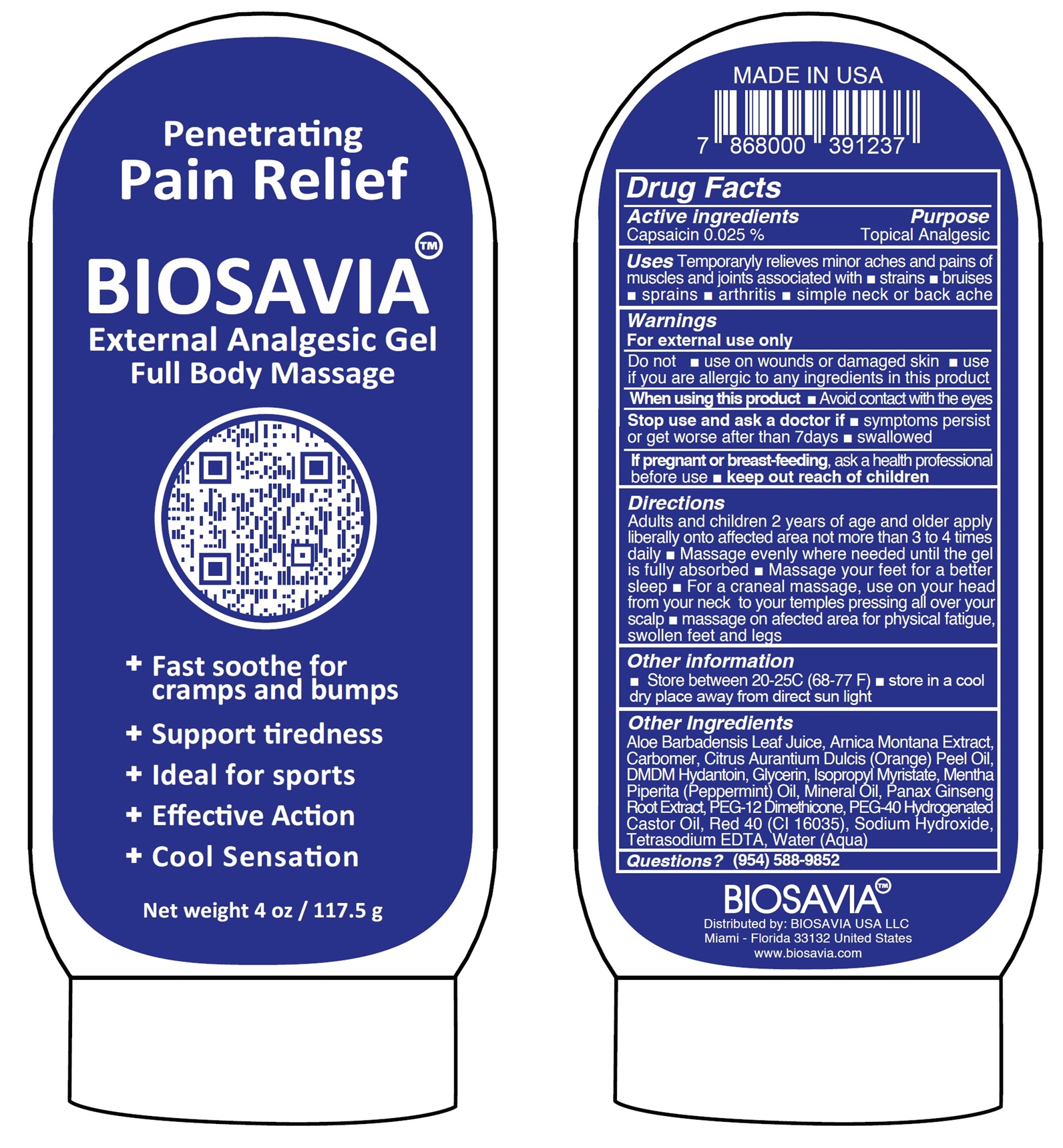 DRUG LABEL: BIOSAVIA External Analgesic Pain Relief
NDC: 84680-529 | Form: GEL
Manufacturer: BIOSAVIA USA, LLC
Category: otc | Type: HUMAN OTC DRUG LABEL
Date: 20240828

ACTIVE INGREDIENTS: CAPSAICIN 0.25 mg/1 g
INACTIVE INGREDIENTS: ALOE VERA LEAF; ARNICA MONTANA WHOLE; CARBOMER HOMOPOLYMER, UNSPECIFIED TYPE; ORANGE OIL, COLD PRESSED; DMDM HYDANTOIN; GLYCERIN; ISOPROPYL MYRISTATE; PEPPERMINT OIL; MINERAL OIL; ASIAN GINSENG; PEG-12 DIMETHICONE; POLYOXYL 40 HYDROGENATED CASTOR OIL; FD&C RED NO. 40; SODIUM HYDROXIDE; EDETATE SODIUM; WATER

BIOSAVIA External Analgesic Pain Relief Gel

Active ingredients

Capsaicin 0.025 %

Purpose

Topical Analgesic

Uses

Temporaryly relieves minor aches and pains of muscles and joints associated with

- strains
- bruises
- sprains
- arthritis
- simple neck or back ache

Warnings

For external use only

Do not

- use on wounds or damaged skin
- use if you are allergic to any ingredients in this product

When using this product

- Avoid contact with the eyes

Stop use and ask a doctor if

- symptoms persist or get worse after than 7days
- swallowed

If pregnant or breast-feeding,

ask a health professional before use

Directions

Adults and children 2 years of age and older apply liberally onto affected area not more than 3 to 4 times daily

- Massage evenly where needed until the gel is fully absorbed
- Massage your feet for a better sleep
- For a craneal massage, use on your head from your neck to your temples pressing all over your scalp
- massage on afected area for physical fatigue, swollen feet and legs

Other information

- Store between 20-25C (68-77 F)
- store in a cool dry place away from direct sun light

Other Ingredients

Aloe Barbadensis Leaf Juice, Arnica Montana Extract, Carbomer, Citrus Aurantium Dulcis (Orange) Peel Oil, DMDM Hydantoin, Glycerin, Isopropyl Myristate, Mentha Piperita (Peppermint) Oil, Mineral Oil, Panax Ginseng Root Extract, PEG-12 Dimethicone, PEG-40 Hydrogenated Castor Oil, Red 40 (CI 16035), Sodium Hydroxide, Tetrasodium EDTA, Water (Aqua)

Questions?

(954) 588-9852